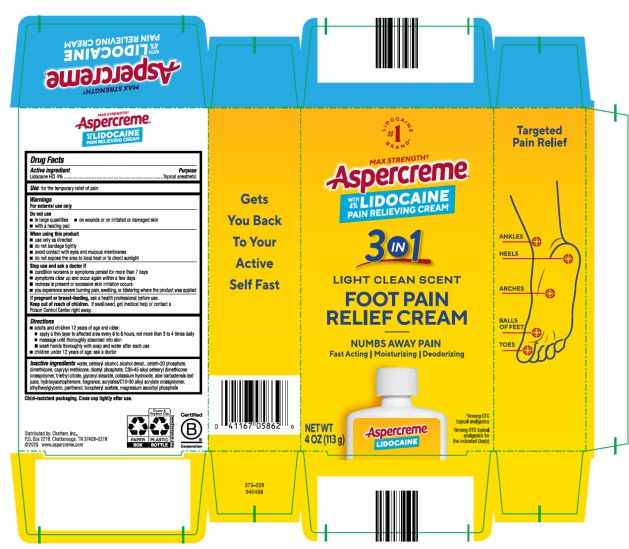 DRUG LABEL: Aspercreme with Lidocaine Foot Pain Creme
NDC: 41167-0586 | Form: CREAM
Manufacturer: Chattem, Inc.
Category: otc | Type: HUMAN OTC DRUG LABEL
Date: 20251219

ACTIVE INGREDIENTS: LIDOCAINE HYDROCHLORIDE 4 g/100 g
INACTIVE INGREDIENTS: WATER; ALCOHOL; CETOSTEARYL ALCOHOL; CETETH-20 PHOSPHATE; DIMETHICONE; CAPRYLYL TRISILOXANE; DIHEXADECYL PHOSPHATE; GLYCERYL MONOSTEARATE; ALOE VERA LEAF; PANTHENOL; ALPHA-TOCOPHEROL ACETATE; MAGNESIUM ASCORBYL PHOSPHATE; AMINOMETHYLPROPANOL; CARBOMER INTERPOLYMER TYPE A (55000 CPS); ETHYLHEXYLGLYCERIN; METHYLPARABEN; EDETATE DISODIUM ANHYDROUS; CITRIC ACID MONOHYDRATE

Aspercreme with Lidocaine Foot Pain Cream

ASPERCREME LIDOCAINE FOOT CREAM

Drug Facts

Active ingredient

Lidocaine HCl 4%

Use

for the temporary relief of pain

Warnings

For external use only

Do not use

■ in large quantities

■ on wounds or on irritated or damaged skin

■ with a heating pad

When using this product

■ use only as directed

■ do not bandage tightly

■ avoid contact with eyes and mucous membranes

■ do not expose the area to local heat or to direct sunlight

Stop use and ask a doctor if

■ condition worsens or symptoms persist for more than 7 days

■ symptoms clear up and occur again within a few days

■ redness is present or excessive skin irritation occurs

■ you experience severe burning pain, swelling, or blistering where the product was applied

If pregnant or breast-feeding,

ask a health professional before use.

Keep out of reach of children.

If swallowed, get medical help or contact a Poison Control Center right away.

Directions

■ adults and children 12 years of age and older:

■ apply a thin layer to affected area every 6 to 8 hours, not more than 3 to 4 times daily

■ massage until thoroughly absorbed into skin

■ wash hands thoroughly with soap and water after each use

■ children under 12 years of age: ask a doctor

Inactive ingredients

water, cetearyl alcohol, alcohol denat., ceteth-20 phosphate, dimethicone, caprylyl methicone, dicetyl phosphate, C30-45 alkyl cetearyl dimethicone crosspolymer, triethyl citrate, glyceryl stearate, potassium hydroxide, aloe barbadensis leaf juice, hydroxyacetophenone, fragrance, acrylates/C10-30 alkyl acrylate crosspolymer, ethylhexylglycerin, panthenol, tocopheryl acetate, magnesium ascorbyl phosphate

Child-resistant packaging. Close cap tightly after use.

PRINCIPAL DISPLAY PANEL

MAX STRENGTH
Aspercreme
WITH 4% LIDOCAINE
PAIN RELIEF CREAM
NET WT 4 OZ (113 g)